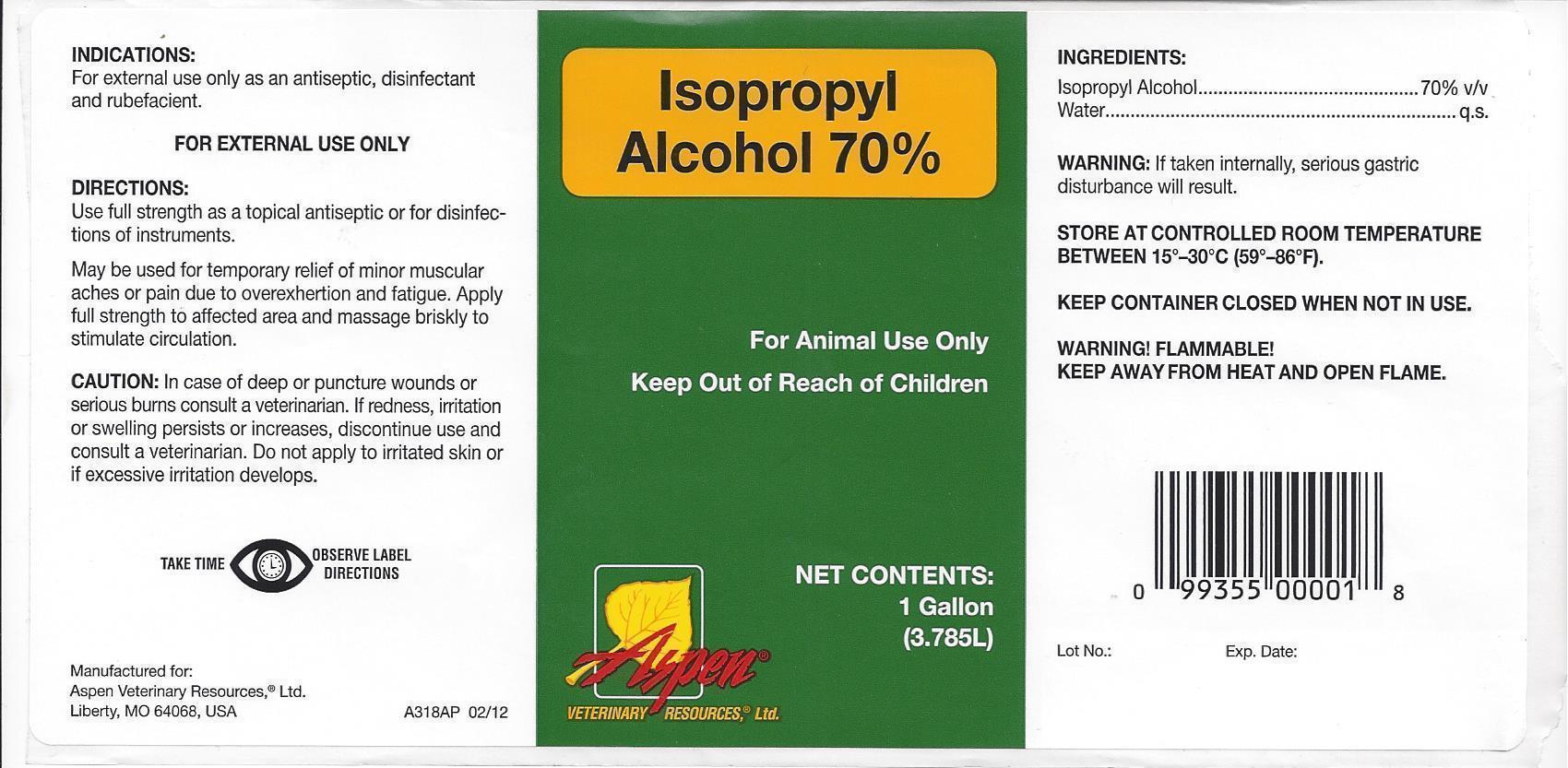 DRUG LABEL: Isopropyl Alcohol
NDC: 46066-004 | Form: LIQUID
Manufacturer: ASPEN VETERINARY
Category: animal | Type: OTC ANIMAL DRUG LABEL
Date: 20131024

ACTIVE INGREDIENTS: ISOPROPYL ALCOHOL 70 mL/100 mL
INACTIVE INGREDIENTS: WATER

Isopropyl Alcohol 70%

Isopropyl Alcohol 70% For Animal Use Only Keep Out of Reach of Children

NET CONTENTS:

1 Gallon

(3.785L)

Aspen

VETERINARY RESOURCES, Ltd.

INDICATIONS:

For external use only as an antiseptic, disinfectant and rubefacient.

FOR EXTERNAL USE ONLY

DIRECTIONS:

Use full strength as a topical antiseptic or for disinfections of instruments.

May be used for temporary relief of minor muscular aches or pain due to overexhertion and fatigue. Apply full strength to affected area and massage briskly to stimulate circulation.

CAUTION:

In case of deep or puncture wounds or serious burns consult a veterinarian. If redness, irritation or swelling persists or increases, discontinue use and consult a veterinarin. Do not apply to irritated skin or if excessive irritation develops.

TAKE TIME OBSERVE LABEL DIRECTIONS

Manufactured for:

Aspen Veterinary Resources, Ltd.

Liberty, MO 64068, USA A318AP 02/12

INGREDIENTS:

ISOPROPYL ALCOHOL………………….70% V/V

WATER………………………………………..q.s.

STORE AT CONTROLLED ROOM TEMPERATURE BETWEEN 15^0-30^0 C (59^0-86^0F).

KEEP CONTAINER CLOSED WHEN NOT IN USE.

WARNING FLAMMABLE!

KEEP AWAY FROM HEAT AND OPEN FLAME.

Lot No.: Exp. Date: